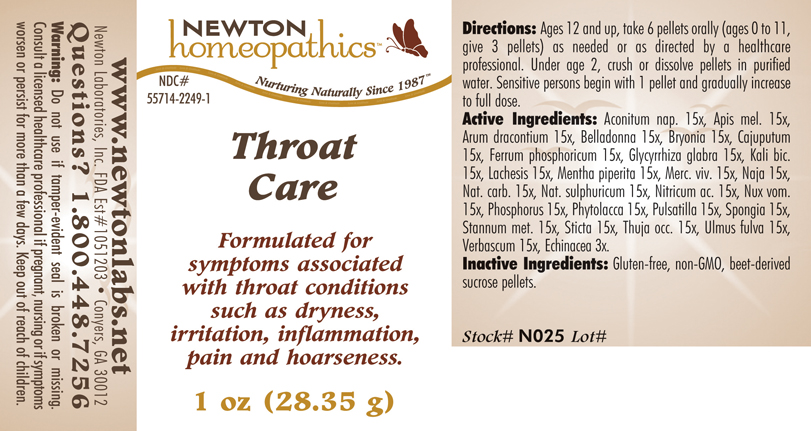 DRUG LABEL: Throat Care 
NDC: 55714-2249 | Form: PELLET
Manufacturer: Newton Laboratories, Inc.
Category: homeopathic | Type: HUMAN OTC DRUG LABEL
Date: 20110301

ACTIVE INGREDIENTS: Aconitum Napellus 15 [hp_X]/1 g; Apis Mellifera 15 [hp_X]/1 g; Arisaema Dracontium Root 15 [hp_X]/1 g; Atropa Belladonna 15 [hp_X]/1 g; Bryonia Alba Root 15 [hp_X]/1 g; Cajuput Oil 15 [hp_X]/1 g; Ferrosoferric Phosphate 15 [hp_X]/1 g; Glycyrrhiza Glabra 15 [hp_X]/1 g; Potassium Dichromate 15 [hp_X]/1 g; Lachesis Muta Venom 15 [hp_X]/1 g; Mentha Piperita 15 [hp_X]/1 g; Mercury 15 [hp_X]/1 g; Naja Naja Venom 15 [hp_X]/1 g; Sodium Carbonate 15 [hp_X]/1 g; Sodium Sulfate 15 [hp_X]/1 g; Nitric Acid 15 [hp_X]/1 g; Strychnos Nux-vomica Seed 15 [hp_X]/1 g; Phosphorus 15 [hp_X]/1 g; Phytolacca Americana Root 15 [hp_X]/1 g; Pulsatilla Vulgaris 15 [hp_X]/1 g; Spongia Officinalis Skeleton, Roasted 15 [hp_X]/1 g; Tin 15 [hp_X]/1 g; Lobaria Pulmonaria 15 [hp_X]/1 g; Thuja Occidentalis Leafy Twig 15 [hp_X]/1 g; Ulmus Rubra Bark 15 [hp_X]/1 g; Verbascum Thapsus 15 [hp_X]/1 g; Echinacea, Unspecified 3 [hp_X]/1 g
INACTIVE INGREDIENTS: Sucrose

Throat Care

INDICATIONS & USAGE SECTION

Throat Care Formulated for symptoms associated with throat conditions such as dryness, irritation, inflammation, pain and hoarseness.

DOSAGE & ADMINISTRATION SECTION

Directions: Ages 12 and up, take 6 pellets orally (ages 0 to 11, give 3 pellets) as needed or as directed by a healthcare professional. Under age 2, crush or dissolve pellets in purfied water. Sensitive persons begin with 1 pellet and gradually increase to full dose.

OTC - ACTIVE INGREDIENT SECTION

Aconitum nap. 15x, Apis mel. 15x, Arum dracontium 15x, Belladonna 15x, Bryonia 15x, Cajuputum 15x, Ferrum phosphoricum 15x, Glycyrrhiza glabra 15x, Kali bic.15x, Lachesis 15x, Mentha piperita 15x, Merc. viv. 15x, Naja 15x, Nat. carb. 15x, Nat. sulphuricum 15x, Nitricum ac. 15x, Nux vom.15x, Phosphorus 15x, Phytolacca 15x, Pulsatilla 15x, Spongia 15x, Stannum met. 15x, Sticta 15x, Thuja occ. 15x, Ulmus fulva 15x, Verbascum 15x, Echinacea 3x.

OTC - PURPOSE SECTION

Formulated for symptoms associated with throat conditions such as dryness, irritation, inflammation, pain and hoarseness.

INACTIVE INGREDIENT SECTION

Inactive Ingredients: Gluten-free, non-GMO, beet-derived sucrose pellets.

QUESTIONS SECTION

www.newtonlabs.net Newton Laboratories, Inc. FDA Est # 1051203 - Conyers, GA 30012
Questions? 1.800.448.7256

WARNINGS SECTION

Warning: Do not use if tamper - evident seal is broken or missing. Consult a licensed healthcare professional if pregnant, nursing or if symptoms worsen or persist for more than a few days. Keep out of reach of children

OTC - PREGNANCY OR BREAST FEEDING SECTION

Consult a licensed healthcare professional if pregnant, nursing or if symptoms worsen or persist for more than a few days.

OTC - KEEP OUT OF REACH OF CHILDREN SECTION

Keep out of reach of children.